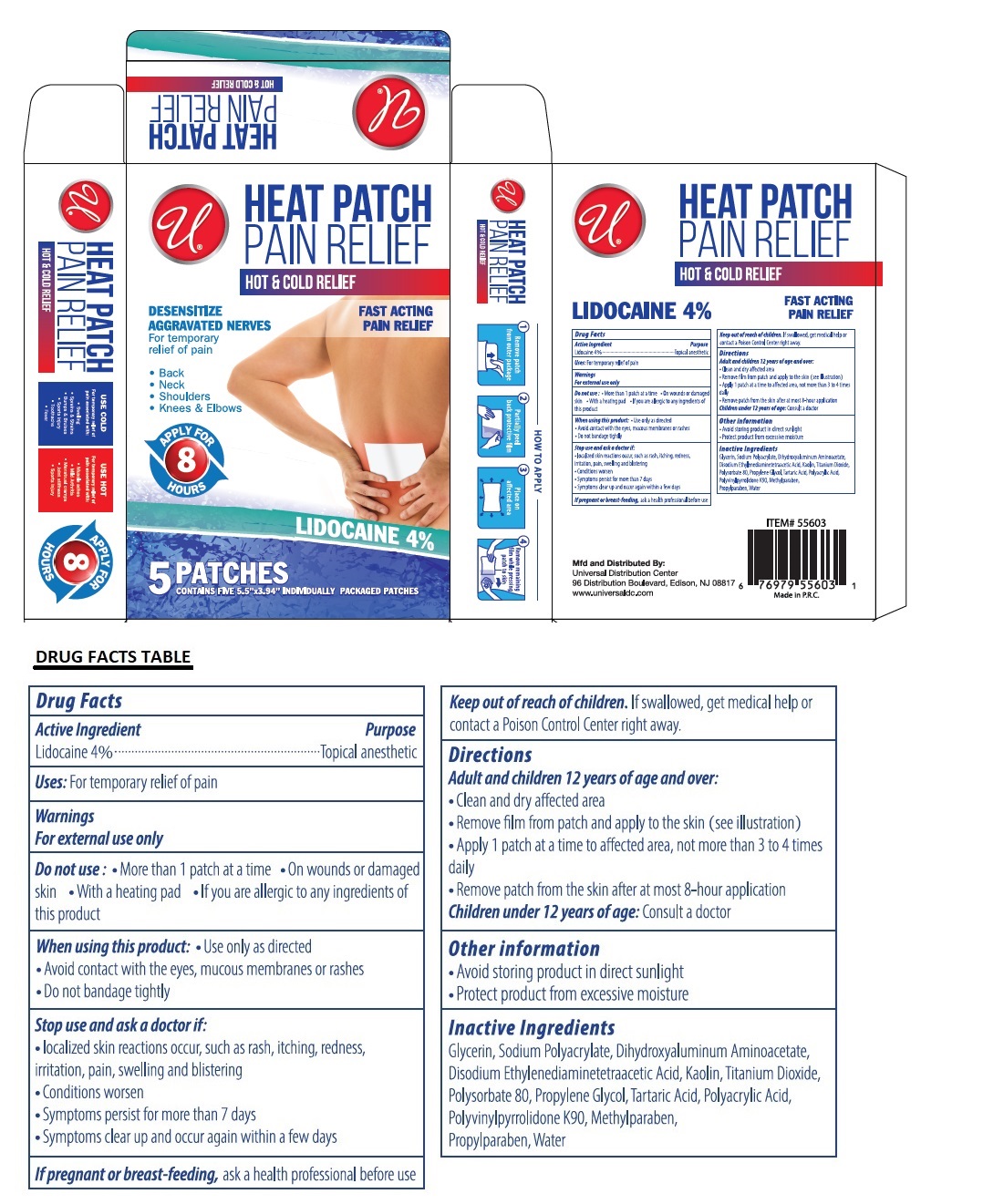 DRUG LABEL: Universal PAIN RELIEF
NDC: 52000-407 | Form: PATCH
Manufacturer: Universal Distribution Center LLC
Category: otc | Type: HUMAN OTC DRUG LABEL
Date: 20241014

ACTIVE INGREDIENTS: LIDOCAINE 0.04 g/1 g
INACTIVE INGREDIENTS: GLYCERIN; SODIUM POLYACRYLATE (2500000 MW); DIHYDROXYALUMINUM AMINOACETATE ANHYDROUS; EDETATE DISODIUM; KAOLIN; TITANIUM DIOXIDE; POLYSORBATE 80; PROPYLENE GLYCOL; TARTARIC ACID; POLYACRYLIC ACID (250000 MW); POVIDONE K90; METHYLPARABEN; PROPYLPARABEN; WATER

Universal HEAT PATCH PAIN RELIEF

Active ingredient

Lidocaine 4%

Purpose

Topical anesthetic

Uses:

For temporary relief of pain

Warnings

For external use only

Do not use: • More than 1 patch at a time • On wounds or damaged skin • With a heating pad • If you are allergic to any ingredients of this product

When using this product: • Use only as directed • Avoid contact with the eyes, mucous membranes or rashes • Do not bandage tightly

Stop use and ask a doctor if: • localized skin reactions occur, such as rash, itching, redness, irritation, pain, swelling and blistering
• Conditions worsen
• Symptoms persists for more than 7 days
• Symptoms clear up and occur again within a few days

If pregnant or breast-feeding, ask a health professional before use

Keep out of reach of children. If swallowed, get medical help or contact a Poison Control Center right away.

Directions

Adult and Children 12 years of age and over:

- Clean and dry affected area
- Remove film from patch and apply to the skin (see illustration)
- Apply 1 patch at a time to affected area, not more than 3 to 4 times daily
- Remove patch from the skin after at most 8-hour application

Children under 12 years of age: Consult a doctor

Other information

- Avoid storing product in direct sunlight
- Protect product from excessive moisture

Inactive ingredients

Glycerin, Sodium Polyacrylate, Dihydroxyaluminum Aminoacetate, Disodium Ethylenediaminetetraacetic Acid, Kaolin, Titanium Dioxide, Polysorbate 80, Propylene Glycol, Tartaric Acid, Polyacrylic Acid, Polyvinylpyrrolidone K90, Methylparaben, Propylparaben, Water

HOT & COLD RELIEF

FAST ACTING
PAIN RELIEF

DESENSITIZE AGGRAVATED NERVES

- Back
- Neck
- Shoulders
- Knees & Elbows

APPLY FOR 8 HOURS

CONTAINS FIVE 5.5"X3.94" INDIVIDUALLY PACKED PATCHES

HOW TO APPLY

1. Remove patch from outer package
2. Partially peel back protective film
3. Place on affected area
4. Remove remaining film while pressing patch to skin

USE COLD

For temporary relief of pain associated with:

- Swelling
- Sprains & Strains
- Bumps & Bruises
- Sports injury
- Toothache
- Fever

USE HOT

For temporary relief of pain associated with:

- Muscle aches
- Mild Arthritis
- Menstrual cramps
- Joint stiffness
- Sports injury

Mfd and Distributed By:
Universal Distribution Center
96 Distribution Boulevard, Edison, NJ 08817
www.universaldc.com

Made in P.R.C